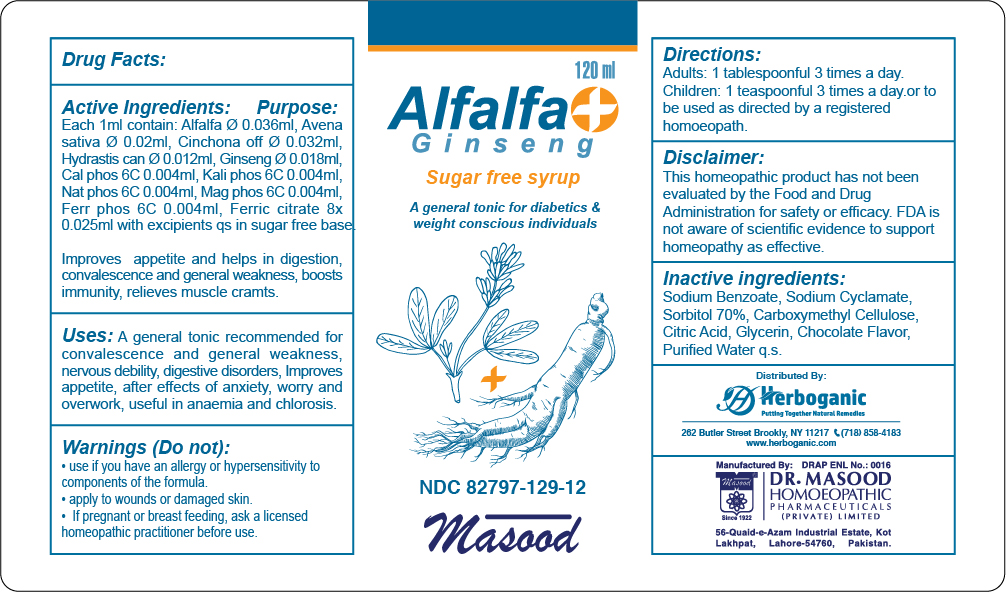 DRUG LABEL: Alfalfa  plus Ginseng Syrup
NDC: 82797-129 | Form: SYRUP
Manufacturer: Dr. Masood Homeopathic Pharmaceuticals Private Limited
Category: homeopathic | Type: HUMAN OTC DRUG LABEL
Date: 20240704

ACTIVE INGREDIENTS: CALCIUM PHOSPHATE 0.48 mg/120 mL; SODIUM PHOSPHATE 0.48 mg/120 mL; CINCHONA OFFICINALIS WHOLE 3.84 mg/120 mL; PANAX GINSENG WHOLE 2.16 mg/120 mL; FERRIC CITRATE ANHYDROUS 3 mg/120 mL; DIBASIC POTASSIUM PHOSPHATE 0.48 mg/120 mL; FERROUS SULFATE 0.48 mg/120 mL; MAGNESIUM PHOSPHATE, DIBASIC TRIHYDRATE 0.48 mg/120 mL; AVENA SATIVA WHOLE 2.4 mg/120 mL; HYDRASTIS CANADENSIS WHOLE 1.44 mg/120 mL; ALFALFA 4.32 mg/120 mL
INACTIVE INGREDIENTS: SODIUM BENZOATE 0.0792 mg/120 mL; SORBITOL SOLUTION 70% 18 mL/120 mL; SODIUM CYCLAMATE 0.24 mg/120 mL; GLYCERIN 18 mL/120 mL; ANHYDROUS CITRIC ACID 0.084 mg/120 mL; CARBOXYMETHYLCELLULOSE 0.78 mg/120 mL

Dosage and Administration

Adults: 1 tablespoonful 3 times a day before meal.

Children: 1 tablespoonful before meal.

OR to be used as directed by a registered Homeopathic practitioner

Indications and Usage

Convalescence, General weakness, Nervous debility, loss of appetite, boost immunity, anemia and chlorosis.

Improves appetite and helps in digestion resulting in improved mental and physical health and weight gain.

Inactive Ingredients

Sodium Benzoate

Sodium Cyclamate

Sorbitol 70 %

Carboxymethyl Cellulose

Citric acid

Glycerin

Water

Active Ingredients

Alfalfa

Cinchona officinalis

Avena sativa

Hydrastis Canadensis

Ginseng

Ferric citrate

Nat phos

Mag phos

Calc phos

Kali phos

Ferrum phos

Keep out of the reach of children

Keep this and all othe rmedicines out of the reach of children

Ingredient Purpose

ALFALFA: Improves appetite and helps in digestion resulting in improved mental and physical health and weight gain

CINCHONA OFF: Helps against exhaustion from general debility

AVENA SATIVA: Convalescence

HYDRASTIS CAN: Improves appetite

GINSENG: Acts as a general tonic, boosts immunity, improves appetite, and increase resistance to infection.

FERRIC CITRATE: It compensates for the generalized weakness of the body due to anemia.

NAT PHOS: Strengthens muscles & bones

MAG PHOS: Helps in relieving muscular cramps

CALC PHOS: for bone development and anemia after acute and chronic wasting diseases

KALI PHOS: Helps in weakness and fatigue

FERR PHOS: Remedy for the first stage of all febrile conditions.

Warnings

Do not:

- use if you have an allergy or hypersensitivity to components of the formula
- apply to wounds or damaged skin

if pregnant or breast feeding, ask a licensed homeopathic practitioner before use